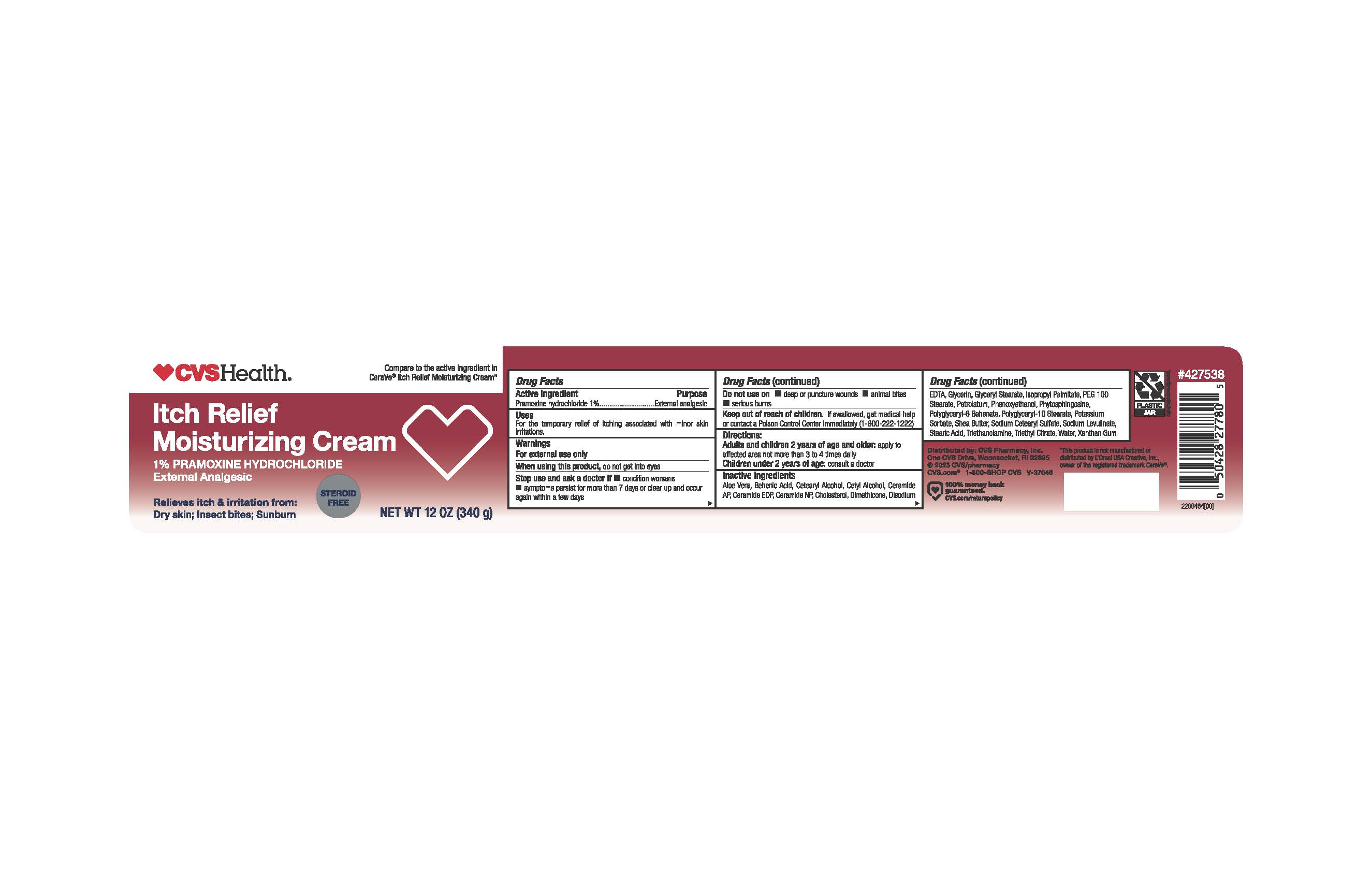 DRUG LABEL: Pramoxine Itch relief
NDC: 51316-141 | Form: CREAM
Manufacturer: CVS
Category: otc | Type: HUMAN OTC DRUG LABEL
Date: 20241211

ACTIVE INGREDIENTS: PRAMOXINE HYDROCHLORIDE 1 g/100 g
INACTIVE INGREDIENTS: GLYCERYL STEARATE/PEG-100 STEARATE; CETOSTEARYL ALCOHOL; EDETATE DISODIUM; XANTHAN GUM; PHENOXYETHANOL; TROLAMINE; CHOLESTEROL; DIMETHICONE; ALOE VERA LEAF; CERAMIDE NP; CERAMIDE 1; CETYL ALCOHOL; PETROLATUM; WHITE PETROLATUM; GLYCERIN; ISOPROPYL PALMITATE; SHEA BUTTER; WATER; CERAMIDE AP; STEARIC ACID

CVS Itch Relief Moisturizing Cream

ACTIVE INGREDIENT

Pramoxine Hydrochloride 1%

PURPOSE

External Analgesic

INDICATIONS AND USAGE

For the temporary relief of itching associated with minor skin irritations

WARNINGS

For external use only

When using this product, do not get into eyes

Stop use and ask a doctor if

- Condition worsens
- symptoms persist for more than 7 days or clear up and occur again within a few days

Do not use on

- deep or puncture wounds
- animal bites
- serious burns

Keep out of reach of children.

If swallowed, get medical help or contact a Poison Control Center immediately (1-800-222-1222)

Directions:

Adults and children 2 years of age and older: apply to affected area not more than 3 to 4 times daily

Children under 2 years of age : consult a doctor

INACTIVE INGREDIENT

Aloe Vera, Behenic Acid, Cetearyl Alcohol, Cetyl Alcohol, Ceramide AP, Ceramide EOP, Ceramide NP, Cholesterol, Dimethicone, Disodium EDTA, Glycerin, Glyceryl Stearate, Isopropyl Palmitate, PEG 100 Stearate, Petrolatum, Phenoxyethanol, Phystosphingosine, Polyglyceryl- 6 Behenate, Polyglyceryl-10 Stearate, Potassium Sorbate, Shea butter, Sodium Cetearyl Sulfate, Sodium Levulinate, Stearic Acid, Triethanolamine, Triethyl Citrate, Water, Xanthan Gum